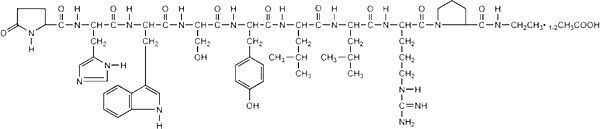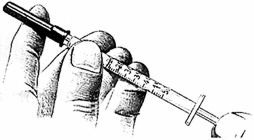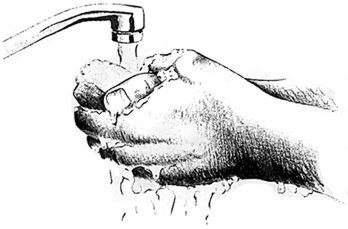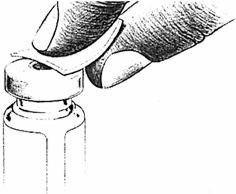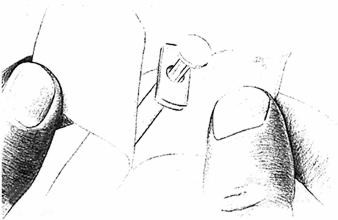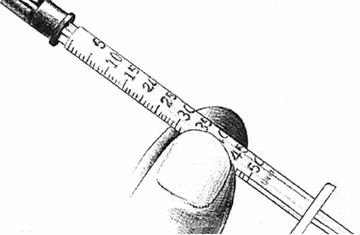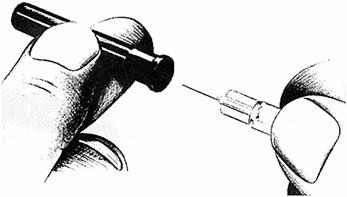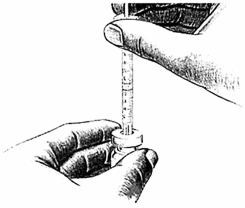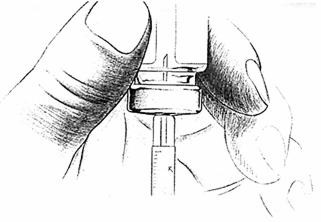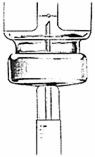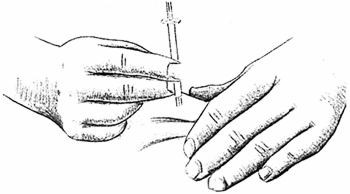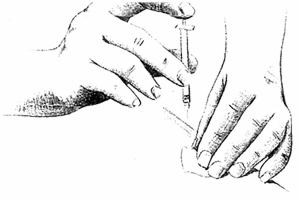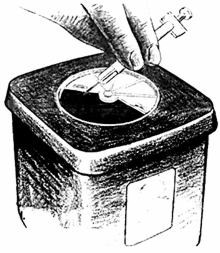 DRUG LABEL: Unknown
Manufacturer: TAP Pharmaceutical Products Inc.
Category: prescription | Type: HUMAN PRESCRIPTION DRUG LABELING
Date: 20080229

LUPRON® INJECTION
(leuprolide acetate)

Rx only

DESCRIPTION

Leuprolide acetate is a synthetic nonapeptide analog of naturally occurring gonadotropin releasing hormone (GnRH or LH-RH). The analog possesses greater potency than the natural hormone. The chemical name is 5-oxo-L-prolyl-L-histidyl-L-tryptophyl-L-seryl-L-tyrosyl-D-leucyl-L-leucyl-L-arginyl-N-ethyl-L-prolinamide acetate (salt) with the following structural formula:

LUPRON INJECTION is a sterile, aqueous solution intended for subcutaneous injection. It is available in a 2.8 mL multiple-dose vial containing leuprolide acetate (5 mg/mL), sodium chloride, USP (6.3 mg/mL) for tonicity adjustment, benzyl alcohol, NF as a preservative (9 mg/mL), and water for injection, USP. The pH may have been adjusted with sodium hydroxide, NF and/or acetic acid, NF.

CLINICAL PHARMACOLOGY

Leuprolide acetate, an LH-RH agonist, acts as a potent inhibitor of gonadotropin secretion when given continuously and in therapeutic doses. Animal and human studies indicate that following an initial stimulation of gonadotropins, chronic administration of leuprolide acetate results in suppression of ovarian and testicular steroidogenesis. This effect is reversible upon discontinuation of drug therapy. Administration of leuprolide acetate has resulted in inhibition of the growth of certain hormone dependent tumors (prostatic tumors in Noble and Dunning male rats and DMBA-induced mammary tumors in female rats) as well as atrophy of the reproductive organs.

In humans, subcutaneous administration of single daily doses of leuprolide acetate results in an initial increase in circulating levels of luteinizing hormone (LH) and follicle stimulating hormone (FSH), leading to a transient increase in levels of the gonadal steroids (testosterone and dihydrotestosterone in males, and estrone and estradiol in pre-menopausal females). However, continuous daily administration of leuprolide acetate results in decreased levels of LH and FSH. In males, testosterone is reduced to castrate levels. In pre-menopausal females, estrogens are reduced to post-menopausal levels. These decreases occur within two to four weeks after initiation of treatment, and castrate levels of testosterone in prostatic cancer patients have been demonstrated for periods of up to five years.

Leuprolide acetate is not active when given orally.

Pharmacokinetics

Absorption

Bioavailability by subcutaneous administration is comparable to that by intravenous administration.

Distribution

The mean steady-state volume of distribution of leuprolide following intravenous bolus administration to healthy male volunteers was 27 L. In vitro binding to human plasma proteins ranged from 43% to 49%.

Metabolism

In healthy male volunteers, a 1 mg bolus of leuprolide administered intravenously revealed that the mean systemic clearance was 7.6 L/h, with a terminal elimination half-life of approximately 3 hours based on a two compartment model. In rats and dogs, administration of ^14C-labeled leuprolide was shown to be metabolized to smaller inactive peptides, a pentapeptide (Metabolite I), tripeptides (Metabolites II and III) and a dipeptide (Metabolite IV). These fragments may be further catabolized.

The major metabolite (M-I) plasma concentrations measured in 5 prostate cancer patients reached maximum concentration 2 to 6 hours after dosing and were approximately 6% of the peak parent drug concentration. One week after dosing, mean plasma M-I concentrations were approximately 20% of mean leuprolide concentrations.

Excretion

Following administration of LUPRON DEPOT 3.75 mg to 3 patients, less than 5% of the dose was recovered as parent and M-I metabolite in the urine.

Special Populations

The pharmacokinetics of the drug in hepatically and renally impaired patients has not been determined.

Drug Interactions

No pharmacokinetic-based drug-drug interaction studies have been conducted with leuprolide acetate. However, because leuprolide acetate is a peptide that is primarily degraded by peptidase and not by cytochrome P-450 enzymes as noted in specific studies, and the drug is only about 46% bound to plasma proteins, drug interactions would not be expected to occur.

CLINICAL STUDIES

In a controlled study comparing LUPRON 1 mg/day given subcutaneously to DES (diethylstilbestrol), 3 mg/day, the survival rate for the two groups was comparable after two years of treatment. The objective response to treatment was also similar for the two groups.

INDICATIONS AND USAGE

LUPRON INJECTION (leuprolide acetate) is indicated in the palliative treatment of advanced prostatic cancer.

CONTRAINDICATIONS

1. LUPRON INJECTION is contraindicated in patients known to be hypersensitive to GnRH, GnRH agonist analogs or any of the excipients in LUPRON INJECTION: Reports of anaphylactic reactions to GnRH agonist analogs have been reported in the medical literature.^1,2
2. LUPRON is contraindicated in women who are or may become pregnant while receiving the drug. LUPRON may cause fetal harm when administered to a pregnant woman. Therefore, the possibility exists that spontaneous abortion may occur if the drug is administered during pregnancy. If this drug is administered during pregnancy or if the patient becomes pregnant while taking any formulation of LUPRON, the patient should be apprised of the potential hazard to the fetus.

WARNINGS

Initially, LUPRON, like other LH-RH agonists, causes increases in serum levels of testosterone. Transient worsening of symptoms, or the occurrence of additional signs and symptoms of prostate cancer, may occasionally develop during the first few weeks of LUPRON treatment. A small number of patients may experience a temporary increase in bone pain, which can be managed symptomatically. As with other LH-RH agonists, isolated cases of ureteral obstruction and spinal cord compression have been observed, which may contribute to paralysis with or without fatal complications.

Safe use of leuprolide acetate in pregnancy has not been established clinically. Before starting treatment with LUPRON, pregnancy must be excluded (see CONTRAINDICATIONS section).

Periodic monitoring of serum testosterone and prostate-specific antigen (PSA) levels is recommended, especially if the anticipated clinical or biochemical response to treatment has not been achieved. It should be noted that results of testosterone determinations are dependent on assay methodology. It is advisable to be aware of the type and precision of the assay methodology to make appropriate clinical and therapeutic decisions.

PRECAUTIONS

Patients with metastatic vertebral lesions and/or with urinary tract obstruction should be closely observed during the first few weeks of therapy (see WARNINGS and ADVERSE REACTIONS sections).

Patients with known allergies to benzyl alcohol, an ingredient of the drug's vehicle, may present symptoms of hypersensitivity, usually local, in the form of erythema and induration at the injection site.

Information for Patients

See INFORMATION FOR PATIENTS which appears after the REFERENCE section.

Laboratory Tests

Response to leuprolide acetate should be monitored by measuring serum levels of testosterone and prostate-specific antigen (PSA). In the majority of patients, testosterone levels increased above baseline during the first week, declining thereafter to baseline levels or below by the end of the second week of treatment. Castrate levels were reached within two to four weeks and once attained were maintained for as long as drug administration continued.

Drug Interactions

See CLINICAL PHARMACOLOGY, Pharmacokinetics section.

Drug/Laboratory Test Interactions

Administration of leuprolide acetate in therapeutic doses results in suppression of the pituitary-gonadal system. Normal function is usually restored within 4 to 12 weeks after treatment is discontinued.

Carcinogenesis, Mutagenesis, Impairment of Fertility

Two-year carcinogenicity studies were conducted in rats and mice. In rats, a dose-related increase of benign pituitary hyperplasia and benign pituitary adenomas was noted at 24 months when the drug was administered subcutaneously at high daily doses (0.6 to 4 mg/kg). There was a significant but not dose-related increase of pancreatic islet-cell adenomas in females and of testicular interstitial cell adenomas in males (highest incidence in the low dose group). In mice no pituitary abnormalities were observed at a dose as high as 60 mg/kg for two years. Patients have been treated with leuprolide acetate for up to three years with doses as high as 10 mg/day and for two years with doses as high as 20 mg/day without demonstrable pituitary abnormalities.

Mutagenicity studies have been performed with leuprolide acetate using bacterial and mammalian systems. These studies provided no evidence of a mutagenic potential.

Clinical and pharmacologic studies in adults (≥ 18 years) with leuprolide acetate and similar analogs have shown full reversibility of fertility suppression when the drug is discontinued after continuous administration for periods of up to 24 weeks. However, no clinical studies have been conducted with leuprolide acetate to assess the reversibility of fertility suppression.

Pregnancy

Teratogenic Effects

Pregnancy Category X

(see CONTRAINDICATIONS and WARNINGS sections)

When administered on day 6 of pregnancy at test dosages of 0.00024, 0.0024, and 0.024 mg/kg (1/600 to 1/6 the human dose) to rabbits, LUPRON produced a dose-related increase in major fetal abnormalities. Similar studies in rats failed to demonstrate an increase in major fetal malformations throughout gestation. There was increased fetal mortality and decreased fetal weights with the two higher doses of LUPRON in rabbits and with the highest dose in rats. The effects on fetal mortality are expected consequences of the alterations in hormonal levels brought about by this drug.

Nursing Mothers

It is not known whether leuprolide acetate is excreted in human milk. LUPRON should not be used by nursing mothers.

Pediatric Use

See labeling for LUPRON INJECTION for Pediatric Use for the safety and effectiveness in children with central precocious puberty.

Geriatric Use

In the clinical trials for LUPRON INJECTION, the majority (69%) of subjects studied were at least 65 years of age. Therefore, the labeling reflects the pharmacokinetics, efficacy and safety of LUPRON in this population.

ADVERSE REACTIONS

Clinical Trials

In the majority of patients testosterone levels increased above baseline during the first week, declining thereafter to baseline levels or below by the end of the second week of treatment. This transient increase was occasionally associated with a temporary worsening of signs and symptoms, usually manifested by an increase in bone pain (see WARNINGS section). In a few cases a temporary worsening of existing hematuria and urinary tract obstruction occurred during the first week. Temporary weakness and paresthesia of the lower limbs have been reported in a few cases.

Potential exacerbations of signs and symptoms during the first few weeks of treatment is a concern in patients with vertebral metastases and/or urinary obstruction which, if aggravated, may lead to neurological problems or increase the obstruction.

In a comparative trial of LUPRON INJECTION (leuprolide acetate) versus DES, in 5% or more of the patients receiving either drug, the following adverse reactions were reported to have a possible or probable relationship to drug as ascribed by the treating physician. Often, causality is difficult to assess in patients with metastatic prostate cancer. Reactions considered not drug related are excluded.

 | LUPRON (N=98) | DES (N=101)
 | Number of Reports
Cardiovascular System
Congestive heart failure | 1 | 5
ECG changes/ischemia | 19 | 22
High blood pressure | 8 | 5
Murmur | 3 | 8
Peripheral edema | 12 | 30
Phlebitis/thrombosis | 2 | 10
Gastrointestinal System
Anorexia | 6 | 5
Constipation | 7 | 9
Nausea/vomiting | 5 | 17
Endocrine System
[Physiologic effect of decreased testosterone.] Decreased testicular size | 7 | 11
Gynecomastia/breast tenderness or pain | 7 | 63
Hot flashes | 55 | 12
Impotence | 4 | 12
Hemic and Lymphatic System
Anemia | 5 | 5
Musculoskeletal System
Bone pain | 5 | 2
Myalgia | 3 | 9
Central/Peripheral Nervous System
Dizziness/lightheadedness | 5 | 7
General pain | 13 | 13
Headache | 7 | 4
Insomnia/sleep disorders | 7 | 5
Respiratory System
Dyspnea | 2 | 8
Sinus congestion | 5 | 6
Integumentary System
Dermatitis | 5 | 8
Urogenital System
Frequency/urgency | 6 | 8
Hematuria | 6 | 4
Urinary tract infection | 3 | 7
Miscellaneous
Asthenia | 10 | 10

In this same study, the following adverse reactions were reported in less than 5% of the patients on LUPRON.

Cardiovascular System—Angina, Cardiac arrhythmias, Myocardial infarction, Pulmonary emboli; Gastrointestinal System—Diarrhea, Dysphagia, Gastrointestinal bleeding, Gastrointestinal disturbance, Peptic ulcer, Rectal polyps; Endocrine System—Libido decrease, Thyroid enlargement; Musculoskeletal System—Joint pain; Central/Peripheral Nervous System—Anxiety, Blurred vision, Lethargy, Memory disorder, Mood swings, Nervousness, Numbness, Paresthesia, Peripheral neuropathy, Syncope/blackouts, Taste disorders; Respiratory System—Cough, Pleural rub, Pneumonia, Pulmonary fibrosis; Integumentary System—Carcinoma of skin/ear, Dry skin, Ecchymosis, Hair loss, Itching, Local skin reactions, Pigmentation, Skin lesions; Urogenital System—Bladder spasms, Dysuria, Incontinence, Testicular pain, Urinary obstruction; Miscellaneous—Depression, Diabetes, Fatigue, Fever/chills, Hypoglycemia, Increased BUN, Increased calcium, Increased creatinine, Infection/inflammation, Ophthalmologic disorders, Swelling (temporal bone).

In an additional clinical trial and from long-term observation of both studies, the following additional adverse events (excluding those considered not drug related) were reported for patients receiving LUPRON.

Cardiovascular System—Bradycardia, Carotid bruit, Extrasystole, Palpitations, Perivascular cuffing (eyes), Ruptured aortic aneurysm, Stroke, Tachycardia, Transient ischemic attack; Gastrointestinal System—Flatus, Dryness of mouth and throat, Hepatitis, Hepatomegaly, Occult blood (rectal exam), Rectal fistula/erythema; Endocrine System—Libido increase, Thyroid nodule; Musculoskeletal System—Ankylosing spondylosis, Arthritis, Blurred disc margins, Bone fracture, Muscle stiffness, Muscle tenderness, Pelvic fibrosis, Spasms/cramps; Central/Peripheral Nervous System—Auditory hallucinations/tinnitus, Decreased hearing, Decreased reflexes, Euphoria, Hyperreflexia, Loss of smell, Motor deficiency; Respiratory System—Chest tightness, Decreased breathing sounds, Hemoptysis, Pleuritic chest pain, Pulmonary infiltrate, Rales/rhonchi, Rhinitis, Strep throat, Wheezing/bronchitis; Integumentary System—Boil (pubic), Bruises, Hives, Keratosis, Mole, Shingles, Spiders; Urogenital System— Blisters on penis, Inguinal hernia, Penile swelling, Post void residual, Prostatic pain, Pyuria; Miscellaneous—Abdominal distention, Facial swelling/edema, Feet burning, Flu, Eyelid growth, Hypoproteinemia, Accidental injury, Knee effusion, Mass, Pallid, Sallow, Weakness.

Postmarketing

During postmarketing surveillance which includes other dosage forms and other patient populations, the following adverse events were reported.

Symptoms consistent with an anaphylactoid or asthmatic process have been rarely (incidence rate of about 0.002%) reported. Rash, urticaria, and photosensitivity reactions have also been reported.

Localized reactions including induration and abscess have been reported at the site of injection.

Symptoms consistent with fibromyalgia (e.g., joint and muscle pain, headaches, sleep disorders, gastrointestinal distress, and shortness of breath) have been reported individually and collectively.

Cardiovascular System – Hypotension, Myocardial infarction; Endocrine System - Diabetes; Gastrointestinal System – Hepatic dysfunction; Hemic and Lymphatic System – Decreased WBC; Integumentary System – Hair growth; Central/Peripheral Nervous System – Spinal fracture/paralysis, Hearing disorder; Miscellaneous – Hard nodule in throat, Weight gain, Increased uric acid; Musculoskeletal System – Tenosynovitis-like symptoms; Respiratory System – Respiratory disorders.

Changes in Bone Density: Decreased bone density has been reported in the medical literature in men who have had orchiectomy or who have been treated with an LH-RH agonist analog. In a clinical trial, 25 men with prostate cancer, 12 of whom had been treated previously with leuprolide acetate for at least six months, underwent bone density studies as a result of pain. The leuprolide-treated group had lower bone density scores than the nontreated control group. It can be anticipated that long periods of medical castration in men will have effects on bone density.

Pituitary apoplexy: During post-marketing surveillance, rare cases of pituitary apoplexy (a clinical syndrome secondary to infarction of the pituitary gland) have been reported after the administration of gonadotropin-releasing hormone agonists. In a majority of these cases, a pituitary adenoma was diagnosed, with a majority of pituitary apoplexy cases occurring within 2 weeks of the first dose, and some within the first hour. In these cases, pituitary apoplexy has presented as sudden headache, vomiting, visual changes, ophthalmoplegia, altered mental status, and sometimes cardiovascular collapse. Immediate medical attention has been required.

See other LUPRON DEPOT and LUPRON INJECTION package inserts for other events reported in the same and different patient populations.

OVERDOSAGE

In rats subcutaneous administration of 250 to 500 times the recommended human dose, expressed on a per body weight basis, resulted in dyspnea, decreased activity, and local irritation at the injection site. There is no evidence at present that there is a clinical counterpart of this phenomenon. In early clinical trials with leuprolide acetate doses as high as 20 mg/day for up to two years caused no adverse effects differing from those observed with the 1 mg/day dose.

DOSAGE AND ADMINISTRATION

The recommended dose is 1 mg (0.2 mL or 20 unit mark) administered as a single daily subcutaneous injection. As with other drugs administered chronically by subcutaneous injection, the injection site should be varied periodically. Each 0.2 mL contains 1 mg of leuprolide acetate, sodium chloride for tonicity adjustment, 1.8 mg of benzyl alcohol as preservative and water for injection. The pH may have been adjusted with sodium hydroxide and/or acetic acid.

Follow the pictorial directions on the reverse side of this package insert for administration.

NOTE: As with all parenteral products, inspect the solution for discoloration and particulate matter before each use.

HOW SUPPLIED

LUPRON INJECTION (leuprolide acetate) is a sterile solution supplied in a 2.8 mL multiple-dose vial. The vial is packaged as follows: 14 Day Patient Administration Kit with 14 disposable syringes and 28 alcohol swabs, NDC 0300-3612-28 and six-vial carton, NDC 0300-3612-24.

Store below 77°F (25°C). Do not freeze. Protect from light; store vial in carton until use.

U.S. Patent Nos. 4,005,063 and 4,005,194.

REFERENCES

1. Taylor, JD. Anaphylactic reaction to LHRH analogue, leuprorelin. Med J Australia 1994 Oct; 161(3): 455.
2. Letterie GS, et al. Recurrent anaphylaxis to a depot form of GnRH analogue. Obstet Gynecol 1991 Nov; 78: 943–946.

SUPPLEMENTAL PATIENT MATERIAL

INFORMATION FOR PATIENTS

Be sure to consult your physician with any questions you may have or for information about LUPRON INJECTION (leuprolide acetate) and its use.

WHAT IS LUPRON?

LUPRON INJECTION (leuprolide acetate) is chemically similar to gonadotropin releasing hormone (GnRH or LH-RH) a hormone which occurs naturally in your body.

Normally, your body releases small amounts of LH-RH and this leads to events which stimulate the production of sex hormones.

However, when you inject LUPRON INJECTION (leuprolide acetate), the normal events that lead to sex hormone production are interrupted and testosterone is no longer produced by the testes.

LUPRON must be injected because, like insulin which is injected by diabetics, LUPRON is inactive when taken by mouth.

If you were to discontinue the drug for any reason, your body would begin making testosterone again.

DIRECTIONS FOR USING LUPRON

1. Wash hands thoroughly with soap and water.
2. If using a new bottle for the first time, flip off the plastic cover to expose the grey rubber stopper. Wipe metal ring and rubber stopper with an alcohol wipe each time you use LUPRON. Check the liquid in the container. If it is not clear or has particles in it, DO NOT USE IT. Exchange it at your pharmacy for another container.
3. Remove outer wrapping from one syringe. Pull plunger back until the tip of the plunger is at the 0.2 mL or 20 unit mark.
4. Take cover off needle. Push the needle through the center of the rubber stopper on the LUPRON bottle.
5. Push the plunger all the way in to inject air into the bottle.
6. Keep the needle in the bottle and turn the bottle upside down. Check to make sure the tip of the needle is in the liquid. Slowly pull back on the plunger, until the syringe fills to the 0.2 mL or 20 unit mark.
7. Toward the end of a two-week period, the amount of LUPRON left in the bottle will be small. Take special care to hold the bottle straight and to keep the needle tip in liquid while pulling back on the plunger.
8. Keeping the needle in the bottle and the bottle upside down, check for air bubbles in the syringe. If you see any, push the plunger slowly in to push the air bubble back into the bottle. Keep the tip of the needle in the liquid and pull the plunger back again to fill to the 0.2 mL or 20 unit mark.
9. Do this again if necessary to eliminate air bubbles.
10. To protect your skin, inject each daily dose at a different body spot.
11. Choose an injection spot. Cleanse the injection spot with another alcohol wipe.
12. Hold the syringe in one hand. Hold the skin taut, or pull up a little flesh with the other hand, as you were instructed.
13. Holding the syringe as you would a pencil, thrust the needle all the way into the skin at a 90° angle. Push the plunger to administer the injection.
14. Hold an alcohol wipe down on your skin where the needle is inserted and withdraw the needle at the same angle it was inserted.
15. Use the disposable syringe only once and dispose of it properly as you were instructed. Needles thrown into a garbage bag could accidentally stick someone. NEVER LEAVE SYRINGES, NEEDLES OR DRUGS WHERE CHILDREN CAN REACH THEM.

SOME SPECIAL ADVICE

- You may experience hot flashes when using LUPRON INJECTION (leuprolide acetate). During the first few weeks of treatment you may experience increased bone pain, increased difficulty in urinating, and less commonly but most importantly, you may experience the onset or aggravation of nerve symptoms. In any of these events, discuss the symptoms with your doctor. Like other treatment options, LUPRON may cause impotence. Notify your doctor if you develop new or worsened symptoms after beginning LUPRON treatment.
- You may experience some irritation at the injection site, such as burning, itching or swelling. These reactions are usually mild and go away. If they do not, tell your doctor.
- If you have experienced an allergic reaction to other drugs like LUPRON, you should not use this drug.
- Do not stop taking your injections because you feel better. You need an injection every day to make sure LUPRON keeps working for you.
- If you need to use an alternate to the syringe supplied with LUPRON, low-dose insulin syringes should be utilized.
- When the drug level gets low, take special care to hold the bottle straight up and down and to keep the needle tip in liquid while pulling back on the plunger.
- Do not try to get every last drop out of the bottle. This will increase the possibility of drawing air into the syringe and getting an incomplete dose. Some extra drug has been provided so that you can withdraw the recommended number of doses.
- Tell your pharmacist when you will need LUPRON so it will be at the pharmacy when you need it.
- Store below 77°F (25°C). Do not store near a radiator or other very warm place. Do not freeze. Protect from light; store vial in carton until use.
- Do not leave your drug or hypodermic syringes where anyone can pick them up.
- Keep this and all other medications out of reach of children.

Manufactured for
TAP Pharmaceuticals Inc.
Lake Forest, IL 60045, U.S.A.

® – Registered
(No. 3612)
03-A066-R7; December 2007
© 1993 – 2007 TAP Pharmaceutical Products Inc.

For Pediatric Use

LUPRON® INJECTION
(leuprolide acetate)

Rx only

DESCRIPTION

Leuprolide acetate is a synthetic nonapeptide analog of naturally occurring gonadotropin releasing hormone (GnRH or LH-RH). The analog possesses greater potency than the natural hormone. The chemical name is 5- oxo -L-prolyl-L-histidyl-L-tryptophyl-L-seryl-L-tyrosyl-D-leucyl-L-leucyl-L-arginyl-N-ethyl-L-prolinamide acetate (salt) with the following structural formula:

LUPRON INJECTION is a sterile, aqueous solution intended for daily subcutaneous injection.

It is available in a 2.8 mL multiple dose vial containing leuprolide acetate (5 mg/mL), sodium chloride, USP (6.3 mg/mL) for tonicity adjustment, benzyl alcohol, NF as a preservative (9 mg/mL), and water for injection, USP. The pH may have been adjusted with sodium hydroxide, NF and/or acetic acid, NF.

CLINICAL PHARMACOLOGY

Leuprolide acetate, a GnRH agonist, acts as a potent inhibitor of gonadotropin secretion when given continuously and in therapeutic doses. Animal and human studies indicate that following an initial stimulation of gonadotropins, chronic administration of leuprolide acetate results in suppression of ovarian and testicular steroidogenesis. This effect is reversible upon discontinuation of drug therapy.

Leuprolide acetate is not active when given orally.

Pharmacokinetics

A pharmacokinetic study of leuprolide acetate in children has not been performed.

Absorption

In adults, bioavailability by subcutaneous administration is comparable to that by intravenous administration.

Distribution

The mean steady-state volume of distribution of leuprolide following intravenous bolus administration to healthy adult male volunteers was 27 L. In vitro binding to human plasma proteins ranged from 43% to 49%.

Metabolism

In healthy adult male volunteers, a 1 mg bolus of leuprolide administered intravenously revealed that the mean systemic clearance was 7.6 L/h, with a terminal elimination half-life of approximately 3 hours based on a two compartment model.

In rats and dogs, administration of ^14C-labeled leuprolide was shown to be metabolized to smaller inactive peptides, a pentapeptide (Metabolite I), tripeptides (Metabolites II and III) and a dipeptide (Metabolite IV). These fragments may be further catabolized.

The major metabolite (M-I) plasma concentrations measured in 5 prostate cancer patients reached maximum concentration 2 to 6 hours after dosing and were approximately 6% of the peak parent drug concentration. One week after dosing, mean plasma M-I concentrations were approximately 20% of mean leuprolide concentrations.

Excretion

Following administration of LUPRON DEPOT 3.75 mg to three adult patients, less than 5% of the dose was recovered as parent and M-I metabolite in the urine.

Special Populations

The pharmacokinetics of the drug in hepatically and renally impaired patients has not been determined.

Drug Interactions

No pharmacokinetic-based drug-drug interaction studies have been conducted with leuprolide acetate. However, because leuprolide acetate is a peptide that is primarily degraded by peptidase and the drug is only about 46% bound to plasma proteins, drug interactions would not be expected to occur.

CLINICAL STUDIES

In children with central precocious puberty (CPP), stimulated and basal gonadotropins are reduced to prepubertal levels. Testosterone and estradiol are reduced to prepubertal levels in males and females respectively. Reduction of gonadotropins will allow for normal physical and psychological growth and development. Natural maturation occurs when gonadotropins return to pubertal levels following discontinuation of leuprolide acetate.

The following physiologic effects have been noted with the chronic administration of leuprolide acetate in this patient population.

1. Skeletal Growth. A measurable increase in body length can be noted since the epiphyseal plates will not close prematurely.
2. Organ Growth. Reproductive organs will return to a prepubertal state.
3. Menses. Menses, if present, will cease.

INDICATIONS AND USAGE

LUPRON INJECTION is indicated in the treatment of children with central precocious puberty. Children should be selected using the following criteria:

1. Clinical diagnosis of CPP (idiopathic or neurogenic) with onset of secondary sexual characteristics earlier than 8 years in females and 9 years in males.
2. Clinical diagnosis should be confirmed prior to initiation of therapy:
  - Confirmation of diagnosis by a pubertal response to a GnRH stimulation test. The sensitivity and methodology of this assay must be understood.
  - Bone age advanced 1 year beyond the chronological age.
3. Baseline evaluation should also include:
  - Height and weight measurements.
  - Sex steroid levels.
  - Adrenal steroid level to exclude congenital adrenal hyperplasia.
  - Beta human chorionic gonadotropin level to rule out a chorionic gonadotropin secreting tumor.
  - Pelvic/adrenal/testicular ultrasound to rule out a steroid secreting tumor.
  - Computerized tomography of the head to rule out intracranial tumor.

CONTRAINDICATIONS

1. Hypersensitivity to GnRH, GnRH agonist analogs or any of the excipients in LUPRON INJECTION. Reports of anaphylactic reactions to GnRH agonist analogs have been reported in the medical literature.^1,2
2. LUPRON is contraindicated in women who are or may become pregnant while receiving the drug. LUPRON may cause fetal harm when administered to a pregnant woman. Major fetal abnormalities were observed in rabbits but not in rats after administration of leuprolide acetate throughout gestation. There was increased fetal mortality and decreased fetal weights in rats and rabbits. (See PRECAUTIONS, Pregnancy, Teratogenic Effects section.) The effects on fetal mortality are expected consequences of the alterations in hormonal levels brought about by this drug. Therefore, the possibility exists that spontaneous abortion may occur if the drug is administered during pregnancy. If this drug is administered during pregnancy or if the patient becomes pregnant while taking any formulation of LUPRON, the patient should be apprised of the potential hazard to the fetus.

WARNINGS

During the early phase of therapy, gonadotropins and sex steroids rise above baseline because of the natural stimulatory effect of the drug. Therefore, an increase in clinical signs and symptoms may be observed (see CLINICAL PHARMACOLOGY section).

Noncompliance with drug regimen or inadequate dosing may result in inadequate control of the pubertal process. The consequences of poor control include the return of pubertal signs such as menses, breast development, and testicular growth. The long-term consequences of inadequate control of gonadal steroid secretion are unknown, but may include a further compromise of adult stature.

PRECAUTIONS

Patients with known allergies to benzyl alcohol, an ingredient of the vehicle of LUPRON INJECTION, may present symptoms of hypersensitivity, usually local, in the form of erythema and induration at the injection site.

Information for Parents

Prior to starting therapy with LUPRON INJECTION, the parent or guardian must be aware of the importance of continuous therapy. Adherence to daily drug administration schedules must be accepted if therapy is to be successful. Irregular dosing could restart the maturation process.

- During the first 2 months of therapy, a female may experience menses or spotting. If bleeding continues beyond the second month, notify the physician.
- Any irritation at the injection site should be reported to the physician immediately. If the child has experienced an allergic reaction to other drugs like LUPRON, this drug should not be used.
- Report any unusual signs or symptoms to the physician, like continued pubertal changes, substantial mood swings or behavioral changes.

Laboratory Tests

Response to leuprolide acetate should be monitored 1-2 months after the start of therapy with a GnRH stimulation test and sex steroid levels. Measurement of bone age for advancement should be done every 6-12 months.

Sex steroids may increase or rise above prepubertal levels if the dose is inadequate (see WARNINGS section). Once a therapeutic dose has been established, gonadotropin and sex steroid levels will decline to prepubertal levels.

Drug Interactions

See CLINICAL PHARMACOLOGY, Pharmacokinetics section.

Drug/Laboratory Test Interactions

Administration of leuprolide acetate in therapeutic doses results in suppression of the pituitary-gonadal system. Normal function is usually restored within 4 to 12 weeks after treatment is discontinued.

Carcinogenesis, Mutagenesis, Impairment of Fertility

A two-year carcinogenicity study was conducted in rats and mice. In rats, a dose-related increase of benign pituitary hyperplasia and benign pituitary adenomas was noted at 24 months when the drug was administered subcutaneously at high daily doses of 0.6 to 4 mg/kg (>100 times the clinical doses of 7.5 to 15 mg/month based on body surface area). There was a significant but not dose-related increase of pancreatic islet-cell adenomas in females and of testes interstitial cell adenomas in males (highest incidence in the low dose group). In mice, no leuprolide acetate-induced tumors or pituitary abnormalities were observed at daily dose as high as 60 mg/kg (>5000 times the clinical doses based on body surface area). Adult patients have been treated with leuprolide acetate for up to three years with doses as high as 10 mg/day and for two years with doses as high as 20 mg/day without demonstrable pituitary abnormalities.

Although no clinical studies have been completed in children to assess the full reversibility of fertility suppression, animal studies (prepubertal and adult rats and monkeys) with leuprolide acetate and other GnRH analogs have shown functional recovery. However, following a study with leuprolide acetate, immature male rats demonstrated tubular degeneration in the testes even after a recovery period. In spite of the failure to recover histologically, the treated males proved to be as fertile as the controls. Also, no histologic changes were observed in the female rats following the same protocol. In both sexes, the offspring of the treated animals appeared normal. The effect of the treatment of the parents on the reproductive performance of the F1 generation was not tested. The clinical significance of these findings is unknown.

Pregnancy

Teratogenic Effects

Pregnancy Category X

(see CONTRAINDICATIONS section)

When administered on day 6 of pregnancy at test dosages of 0.00024, 0.0024, and 0.024 mg/kg (1/1200 to 1/12 the human pediatric dose) to rabbits, LUPRON produced a dose-related increase in major fetal abnormalities. Similar studies in rats failed to demonstrate an increase in fetal malformations. There was increased fetal mortality and decreased fetal weights with the two higher doses of LUPRON in rabbits and with the highest dose in rats.

Nursing Mothers

It is not known whether leuprolide acetate is excreted in human milk. LUPRON should not be used by nursing mothers.

Geriatric Use

See labeling for LUPRON INJECTION for the pharmacokinetics, efficacy and safety of LUPRON in this population.

ADVERSE REACTIONS

Clinical Trials

Potential exacerbation of signs and symptoms during the first few weeks of treatment (see PRECAUTIONS section) is a concern in patients with rapidly advancing central precocious puberty.

In two studies of children with central precocious puberty, in 2% or more of the patients receiving the drug, the following adverse reactions were reported to have a possible or probable relationship to drug as ascribed by the treating physician. Reactions considered not drug related are excluded.

 | Number of Patients N = 395 (Percent)
Body as a Whole
General Pain | 7 | (2)
Integumentary System
Acne/Seborrhea | 7 | (2)
Injection Site Reactions Including Abscess | 21 | (5)
Rash Including Erythema Multiforme | 8 | (2)
Urogenital System
Vaginitis/Bleeding/ Discharge | 7 | (2)

In those same studies, the following adverse reactions were reported in less than 2% of the patients.

Body as a Whole - Body Odor, Fever, Headache, Infection; Cardiovascular System - Syncope, Vasodilation; Digestive System - Dysphagia, Gingivitis, Nausea/Vomiting; Endocrine System - Accelerated Sexual Maturity; Metabolic and Nutritional Disorders - Peripheral Edema, Weight Gain; Nervous System - Nervousness, Personality Disorder, Somnolence, Emotional Lability; Respiratory System - Epistaxis; Integumentary System - Alopecia, Skin Striae; Urogenital System - Cervix Disorder, Gynecomastia/Breast Disorders, Urinary Incontinence.

Postmarketing

During postmarketing surveillance, which includes other dosage forms and other patient populations, the following adverse events were reported.

Symptoms consistent with an anaphylactoid or asthmatic process have been rarely (incidence rate of about 0.002%) reported. Rash, urticaria, and photosensitivity reactions have also been reported. Localized reactions including induration and abscess have been reported at the site of injection. Symptoms consistent with fibromyalgia (e.g., joint and muscle pain, headaches, sleep disorders, gastrointestinal distress, and shortness of breath) have been reported individually and collectively.

Cardiovascular System – Hypotension, Pulmonary embolism; Gastrointestinal System – Hepatic dysfunction; Hemic and Lymphatic System – Decreased WBC; Integumentary System – Hair growth; Central/Peripheral Nervous System – Peripheral neuropathy, Spinal fracture/paralysis, Hearing disorder; Miscellaneous – Hard nodule in throat, Weight gain, Increased uric acid; Musculoskeletal System – Tenosynovitis-like symptoms; Respiratory System – Respiratory disorders; Urogenital System – Prostate pain.

Changes in Bone Density: Decreased bone density has been reported in the medical literature in men who have had orchiectomy or who have been treated with an LH-RH agonist analog. In a clinical trial, 25 men with prostate cancer, 12 of whom had been treated previously with leuprolide acetate for at least six months, underwent bone density studies as a result of pain. The leuprolide-treated group had lower bone density scores than the nontreated control group. The effects on bone density in children are unknown.

Pituitary apoplexy: During post-marketing surveillance, rare cases of pituitary apoplexy (a clinical syndrome secondary to infarction of the pituitary gland) have been reported after the administration of gonadotropin-releasing hormone agonists. In a majority of these cases, a pituitary adenoma was diagnosed, with a majority of pituitary apoplexy cases occurring within 2 weeks of the first dose, and some within the first hour. In these cases, pituitary apoplexy has presented as sudden headache, vomiting, visual changes, ophthalmoplegia, altered mental status, and sometimes cardiovascular collapse. Immediate medical attention has been required.

See other LUPRON INJECTION and LUPRON DEPOT package inserts for adverse events reported in other patient populations.

OVERDOSAGE

In rats, subcutaneous administration of 125 to 250 times the recommended human pediatric dose, expressed on a per body weight basis, resulted in dyspnea, decreased activity, and local irritation at the injection site. There is no evidence at present that there is a clinical counterpart of this phenomenon. In early clinical trials using leuprolide acetate in adult patients, doses as high as 20 mg/day for up to two years caused no adverse effects differing from those observed with the 1 mg/day dose.

DOSAGE AND ADMINISTRATION

LUPRON INJECTION can be administered by a patient/parent or health care professional.

The dose of LUPRON INJECTION must be individualized for each child. The dose is based on a mg/kg ratio of drug to body weight. Younger children require higher doses on a mg/kg ratio.

After 1-2 months of initiating therapy or changing doses, the child must be monitored with a GnRH stimulation test, sex steroids, and Tanner staging to confirm downregulation. Measurements of bone age for advancement should be monitored every 6-12 months. The dose should be titrated upward until no progression of the condition is noted either clinically and/or by laboratory parameters.

The first dose found to result in adequate downregulation can probably be maintained for the duration of therapy in most children. However, there are insufficient data to guide dosage adjustment as patients move into higher weight categories after beginning therapy at very young ages and low dosages. It is recommended that adequate downregulation be verified in such patients whose weight has increased significantly while on therapy.

As with other drugs administered by injection, the injection site should be varied periodically.

Discontinuation of LUPRON INJECTION should be considered before age 11 for females and age 12 for males.

The recommended starting dose is 50 mcg/kg/day administered as a single subcutaneous injection. If total downregulation is not achieved, the dose should be titrated upward by 10 mcg/kg/day. This dose will be considered the maintenance dose.

Follow the pictorial directions on the reverse side of this package insert for administration.

NOTE: As with other parenteral products, inspect the solution for discoloration and particulate matter before each use.

HOW SUPPLIED

LUPRON INJECTION (leuprolide acetate) is a sterile solution supplied in a 2.8 mL multiple-dose vial. The vial is packaged as follows:

- 14 Day Patient Administration Kit with 14 disposable syringes and 28 alcohol swabs, NDC 0300-3612-28.
- Six-vial carton, NDC 0300-3612-24.
- Store below 77°F (25°C). Do not freeze. Protect from light; store vial in carton until use.
- Use the syringes supplied with LUPRON INJECTION. Insulin syringes may be substituted for use with LUPRON INJECTION.

U.S. Patent Nos. 4,005,063; 4,005,194.

REFERENCES

1. Taylor, JD. Anaphylactic reaction to LHRH analogue, leuprorelin. Med J Australia 1994 Oct; 161(3): 455.
2. Letterie GS, et al. Recurrent anaphylaxis to a depot form of GnRH analogue. Obstet Gynecol 1991 Nov; 78: 943–946.

Manufactured for
TAP Pharmaceuticals Inc.
Lake Forest, IL 60045, U.S.A.

® – Registered

(No. 3612)

ADMINISTERING THE INJECTION

Read this booklet before injecting the medication. Read the complete instructions for injection.

TAP Pharmaceutical Products Inc.
Lake Forest, IL 60045, U.S.A.

(No. 3612)
03-A066 R7; December 2007

© 1993–2007 TAP Pharmaceutical Products Inc.

Provided as an educational service by
TAP Pharmaceuticals Inc.

TAP Pharmaceutical Products Inc.
Lake Forest, IL 60045, U.S.A.

[Bar code 128 of commodity number]

SUPPLEMENTAL PATIENT MATERIAL

ADMINISTERING THE INJECTION

1. Wash hands thoroughly.
2. Check the liquid in the container. It should look clear. DO NOT USE if it is not clear or if it has particles in it. If using a new bottle, flip off the plastic cover to expose the grey rubber stopper. Use an alcohol swab to cleanse the metal ring and rubber stopper on medication bottle every day, just before you use it.
3. Remove outer wrapping from one syringe.
4. Pull the syringe plunger back until its tip is at the proper mark.
5. Uncover needle. Do not touch the needle.
6. Place the bottle on a clean, flat surface and push the needle through the center of the rubber stopper on the bottle. Push the plunger all the way in to inject air into the bottle.
7. Keep the needle in the bottle.
  Lift the bottle and turn it straight upside down.
  Check to see that the needle tip is in the liquid.
8. With the needle tip in the liquid, slowly pull back the plunger until syringe fills to the proper mark.
  If any bubbles appear in the syringe, remove them by pushing the plunger up slowly.
  With the needle tip still in the liquid, pull the plunger until it is once more at the proper mark.
9. Choose a different injection site each day.
  Cleanse the injection site with a new alcohol swab.
  Hold the skin the way you were instructed.
  Slide the needle quickly all the way through the skin, into the subcutaneous tissue, at a 90° angle.
10. Push the plunger to inject the medication.
  Withdraw the needle at the same angle it was inserted (90°).
  Wipe the skin with an alcohol swab.
11. Dispose of the syringe and alcohol swabs as you were instructed.
  Remember: use the disposable syringe only once.